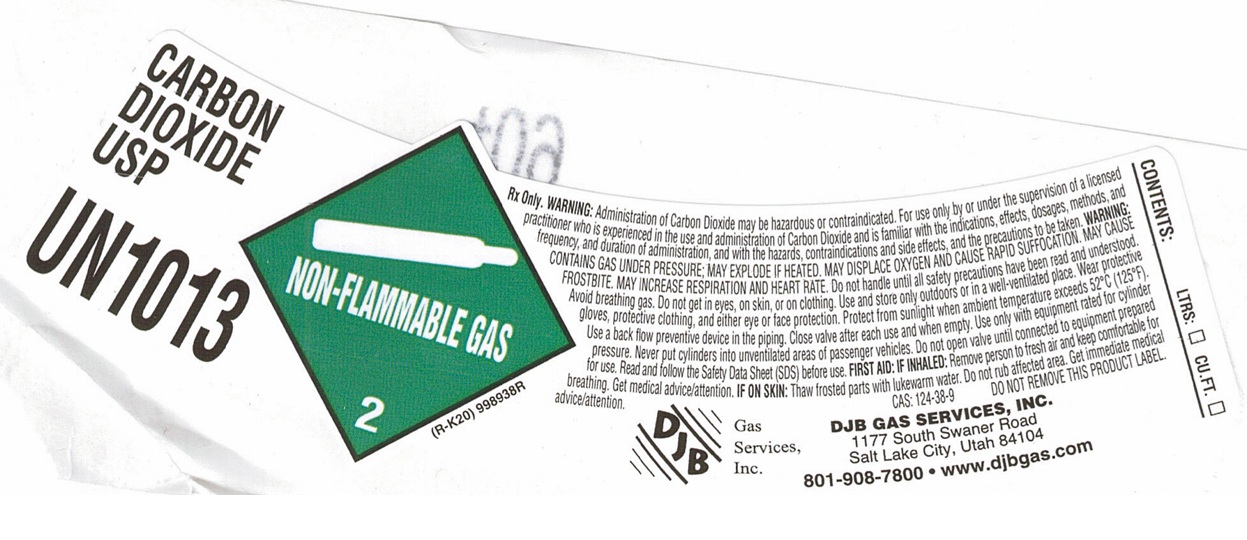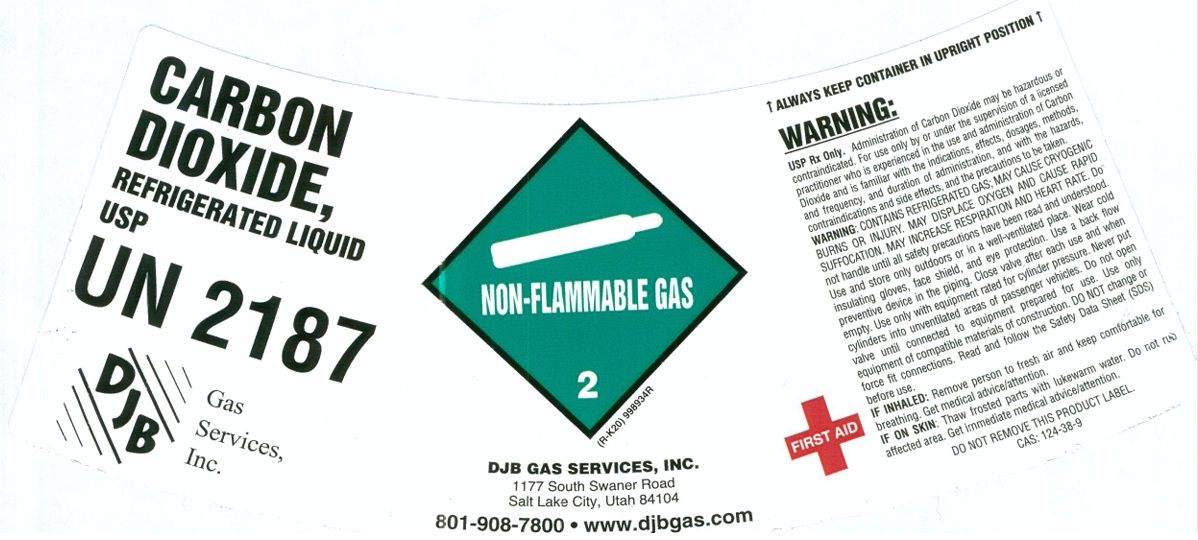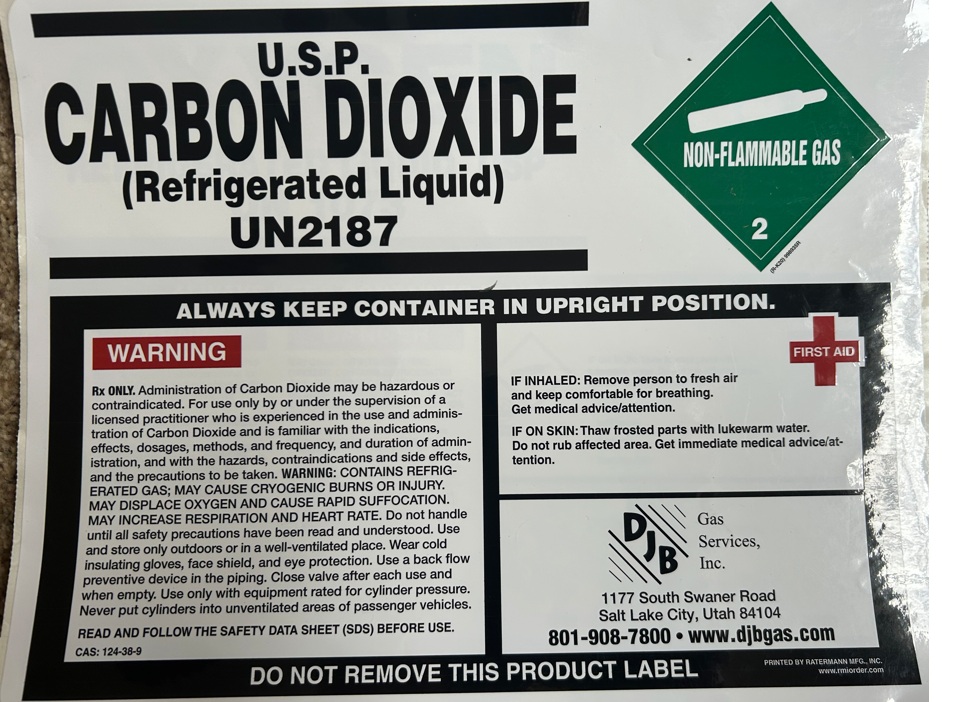 DRUG LABEL: Carbon Dioxide
NDC: 43621-007 | Form: GAS
Manufacturer: DJB Gas Services, Inc
Category: prescription | Type: HUMAN PRESCRIPTION DRUG LABEL
Date: 20250224

ACTIVE INGREDIENTS: CARBON DIOXIDE 990 mL/1 L

Carbon Dioxide

PACKAGE LABEL

CARBON DIOXIDE USP

UN1013

Rx Only. WARNING: Administration of Carbon Dioxide may be hazardous or contraindicated. For use only by or under the supervision of a licensed practitioner who is experienced in the use and administration of Carbon Dioxide and is familiar with the indications, effects, dosages, methods, and frequency, and duration of administration, and with the hazards, contraindications and side effects, and the precautions to be taken. WARNING: CONTAINS GAS UNDER PRESSURE; MAY EXPLODE IF HEATED. MAY DISPLACE OXYGEN AND CAUSE RAPID SUFFOCATION. MAY CAUSE FROSTBITE. MAY INCREASE RESPIRATION AND HEART RATE. Do not handle until all safety precautions have been read and understood. Avoid breathing gas. Do not get in eyes, on skin, or on clothing. Use and store only outdoors or in a well-ventilated place. Wear protective gloves, protective clothing, and either eye or face protection. Protect from sunlight when ambient temperature exceeds 52 C (125 F). Use a back flow preventive device in the piping. Close valve after each use and when empty. Use only with equipment rated for cylinder pressure. Never put cylinders into unventilated areas of passenger vehicles. Do not open valve until connected to equipment prepared for use. Read and follow the Safety Data Sheet (SDS) before use. FIRST AID: IF INHALED: Remove person to fresh air and keep comfortable for breathing. Get medical advice/attention. IF ON SKIN: Thaw frosted parts with lukewarm water. Do not rub affected area. Get immediate medical advice/attention. CAS: 124-38-9 DO NOT REMOVE THIS PRODUCT LABEL.

DJB Gas Services, Inc.

DJB GAS SERVICES, INC.

1177 Swaner Road

Salt Lake City, UT 84104

801-908-7800 www.djbgas.com

CONTENTS: LTRS: CU.FT.

PACKAGE LABEL

CARBON DIOXIDE, REFRIGERATED LIQUID USP

UN 2187

DJB Gas Services, Inc.

DJB GAS SERVICES, INC.

1177 Swaner Road

Salt Lake City, UT 84104

801-908-7800 www.djbgas.com

ALWAYS KEEP CONTAINER IN UPRIGHT POSITION

WARNING: USP Rx Only. Administration of Carbon Dioxide may be hazardous or contraindicated. For use only by or under the supervision of a licensed practitioner who is experienced in the use and administration of Carbon Dioxide and is familiar with the indications, effects, dosages, methods, and frequency, and duration of administration, and with the hazards, contraindications and side effects, and the precautions to be taken.

WARNING: CONTAINS REFRIGERATED GAS; MAY CAUSE CRYOGENIC BURNS OR INJURY. MAY DISPLACE OXYGEN AND CAUSE RAPID SUFFOCATION. MAY INCREASE RESPIRATION AND HEART RATE. Do not handle until all safety precautions have been read and understood. Use and store only outdoors or in a well-ventilated place. Wear cold insulating gloves, face shield, and eye protection. Use a back flow preventive device in the piping. Close valve after each use and when empty. Use only with equipment rated for cylinder pressure. Never put cylinders into unventilated areas of passenger vehicles. Do not open valve until connected to equipment prepared for use. Use only equipment of compatible materials of construction. DO NOT change or force fit connections. Read and follow the Safety Data Sheet (SDS) before use.

FIRST AID IF INHALED: Remove person to fresh air and keep comfortable for breathing. Get medical advice/attention.

IF ON SKIN: Thaw frosted parts with lukewarm water. Do not rub affected area. Get immediate medical advice/attention.

DO NOT REMOVE THIS PRODUCT LABEL.

CAS: 124-38-9

PACKAGE LABEL

U.S.P. CARBON DIOXIDE (Refrigerated Liquid)

UN2187

ALWAYS KEEP CONTAINER IN UPRIGHT POSITION.

WARNING

Rx ONLY. Administration of Carbon Dioxide may be hazardous or contraindicated. For use only by or under the supervision of a licensed practitioner who is experienced in the use and administration of Carbon Dioxide and is familiar with the indications, effects, dosages, methods, and frequency, and duration of administration, and with the hazards, contraindications and side effects, and the precautions to be taken. WARNING: CONTAINS REFRIGERATED GAS; MAY CAUSE CRYOGENIC BURNS OR INJURY. MAY DISPLACE OXYGEN AND CAUSE RAPID SUFFOCATION. MAY INCREASE RESPIRATION AND HEART RATE. Do not handle until all safety precautions have been read and understood. Use and store only outdoors or in a well-ventilated place. Wear cold insulating gloves, face shield, and eye protection. Use a back flow preventive device in the piping. Close valve after each use and when empty. Use only with equipment rated for cylinder pressure. Never put cylinder into unventilated areas of passenger vehicles.

READ AND FOLLOW THE SAFETY DATA SHEET (SDS) BEFORE USE.

CAS: 124-38-9

FIRST AID

IF INHALED: Remove person to fresh air and keep comfortable for breathing. Get medical advice/attention.

IF ON SKIN: Thaw frosted parts with lukewarm water. Do not rub affected area. Get immediate medical advice/attention.

DJB Gas Services, Inc.

1177 Swaner Road

Salt Lake City, UT 84104

801-908-7800 www.djbgas.com